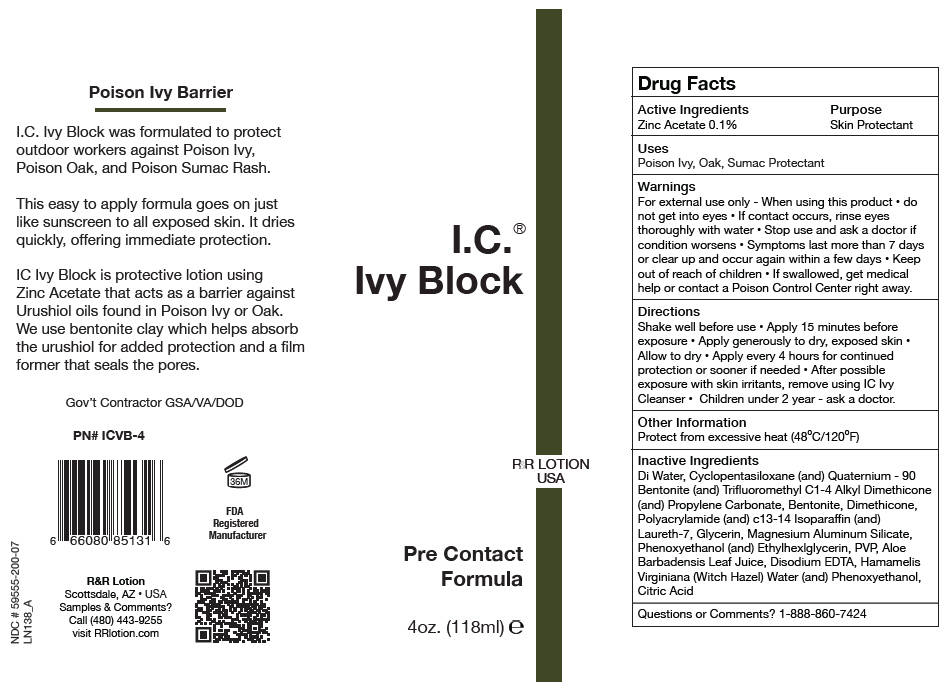 DRUG LABEL: I.C. Ivy Block
NDC: 59555-200 | Form: LOTION
Manufacturer: R & R Lotion, Inc
Category: otc | Type: HUMAN OTC DRUG LABEL
Date: 20250910

ACTIVE INGREDIENTS: ZINC ACETATE 1 mg/1 mL
INACTIVE INGREDIENTS: CYCLOMETHICONE 5; QUATERNIUM-90; BENTONITE; DIMETHICONE, UNSPECIFIED; PROPYLENE CARBONATE; POLYACRYLAMIDE (10000 MW); C13-14 ISOPARAFFIN; LAURETH-7; GLYCERIN; MAGNESIUM ALUMINUM SILICATE; PHENOXYETHANOL; ETHYLHEXYLGLYCERIN; POVIDONE, UNSPECIFIED; ALOE VERA LEAF JUICE; EDETATE DISODIUM; HAMAMELIS VIRGINIANA TOP WATER; CITRIC ACID MONOHYDRATE

I.C.® Ivy Block

Drug Facts

Active Ingredients

Zinc Acetate 0.1%

Purpose

Skin Protectant

Uses

Poison Ivy, Oak, Sumac Protectant

Warnings

For external use only - When using this product

- do not get into eyes
- If contact occurs, rinse eyes thoroughly with water
- Stop use and ask a doctor if condition worsens
- Symptoms last more than 7 days or clear up and occur again within a few days

- Keep out of reach of children
- If swallowed, get medical help or contact a Poison Control Center right away.

Directions

Shake well before use

- Apply 15 minutes before exposure
- Apply generously to dry, exposed skin
- Allow to dry
- Apply every 4 hours for continued protection or sooner if needed
- After possible exposure with skin irritants, remove using IC Ivy Cleanser
- Children under 2 year - ask a doctor.

Other Information

Protect from excessive heat (48°C/120°F)

Inactive Ingredients

Di Water, Cyclopentasiloxane (and) Quaternium - 90 Bentonite (and) Trifluoromethyl C1-4 Alkyl Dimethicone (and) Propylene Carbonate, Bentonite, Dimethicone, Polyacrylamide (and) c13-14 Isoparaffin (and) Laureth-7, Glycerin, Magnesium Aluminum Silicate, Phenoxyethanol (and) Ethylhexlglycerin, PVP, Aloe Barbadensis Leaf Juice, Disodium EDTA, Hamamelis Virginiana (Witch Hazel) Water (and) Phenoxyethanol, Citric Acid

Questions or Comments?

1-888-860-7424

PRINCIPAL DISPLAY PANEL - 118 ml Bottle Label

I.C.®
Ivy Block

R&R LOTION
USA

Pre Contact
Formula

4oz. (118ml) ℮